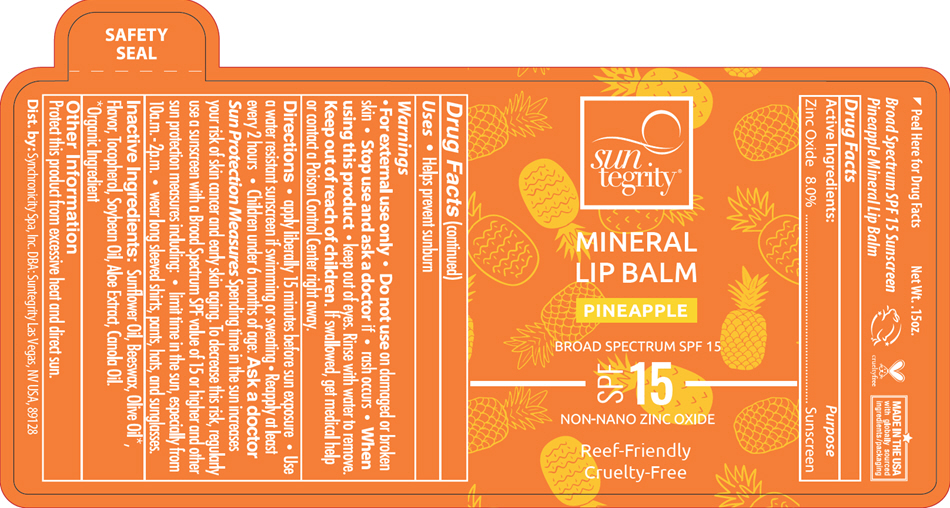 DRUG LABEL: Mineral Lip Balm 
NDC: 69949-559 | Form: STICK
Manufacturer: Synchronicity Spa, Inc. DBA Suntegrity
Category: otc | Type: HUMAN OTC DRUG LABEL
Date: 20251017

ACTIVE INGREDIENTS: Zinc Oxide 0.34 g/4.25 g
INACTIVE INGREDIENTS: SUNFLOWER OIL; WHITE WAX; OLIVE OIL; TOCOPHEROL; SOYBEAN OIL; ALOE VERA LEAF; CANOLA OIL

Mineral Lip Balm
Pineapple

Drug Facts

Active Ingredients

Zinc Oxide 8.0%

Purpose

Sunscreen

Uses

- Helps prevent sunburn

Warnings

- For external use only

- Do not use on damaged or broken skin

- Stop use and ask a doctor if – rash occurs

- When using this product – keep out of eyes. Rinse with water to remove.

- Keep out of reach of children. If swallowed, get medical help or contact a Poison Control Center right away.

Directions

- Apply liberally 15 minutes before sun exposure
- Use a water resistant sunscreen if swimming or sweating
- Reapply at least every 2 hours
- Children under 6 months of age: Ask a doctor

Sun Protection Measures Spending time in the sun increases your risk of skin cancer and early skin aging. To decrease this risk, regularly use a sunscreen with a Broad Spectrum SPF value of 15 or higher and other sun protection measures including:

- limit time in the sun, especially from 10a.m. – 2p.m.
- wear long sleeved shirts, pants, hats, and sunglasses.

Inactive Ingredients

Sunflower Oil, Beeswax, Olive Oil [Organic Ingredient] , Flavor, Tocopherol, Soybean Oil, Aloe Extract, Canola Oil.

Other Information

Protect this product from excessive heat and direct sun.

STORAGE AND HANDLING

Dist. By: Synchronicity Spa, Inc. DBA: Suntegrity Las Vegas, NV USA, 89128

PRINCIPAL DISPLAY PANEL - 4.25 g Tube Label

sun
tegrity®

MINERAL
LIP BALM

PINEAPPLE

BROAD SPECTRUM SPF 15

SPF 15

NON-NANO ZINC OXIDE

Reef-Friendly
Cruelty-Free